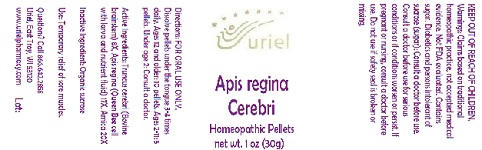 DRUG LABEL: Apis regina Cerebri
NDC: 48951-1062 | Form: PELLET
Manufacturer: Uriel Pharmacy Inc.
Category: homeopathic | Type: HUMAN OTC DRUG LABEL
Date: 20180531

ACTIVE INGREDIENTS: BOS TAURUS BRAINSTEM 8 [hp_X]/1 1; ROYAL JELLY 17 [hp_X]/1 1; ARNICA MONTANA ROOT 20 [hp_X]/1 1
INACTIVE INGREDIENTS: SUCROSE

Apis regina Cerebri

INDICATIONS AND USAGE

Directions: FOR ORAL USE ONLY.

DOSAGE AND ADMINISTRATION

Dissolve pellets under the tongue 3-4 times daily. Ages 12 and older: 10 pellets. Ages 2-11: 5 pellets. Under age 2: Consult
a doctor.

ACTIVE INGREDIENT

Active Ingredients: Truncus cerebri (Bovine brainstem) 8X, Apis regina (Queen Bee cell with larva and nutrient fluid) 17X, Arnica 20X

Inactive Ingredient: Sucrose

PURPOSE

Use: Temporary relief of sore muscles.

KEEP OUT OF REACH OF CHILDREN.

WARNINGS

Warnings: Claims based on traditional homeopathic practice, not accepted medical evidence. Not FDA evaluated. Contains sugar. Diabetics and persons intolerant of sucrose (sugar): Consult a doctor before use. Consult a doctor before use for serious conditions or if conditions worsen or persist. If pregnant or nursing, consult a doctor before use. Do not use if safety seal is broken or missing.

Questions? Call 866.642.2858
Uriel, East Troy, WI 53120
www.urielpharmacy.com